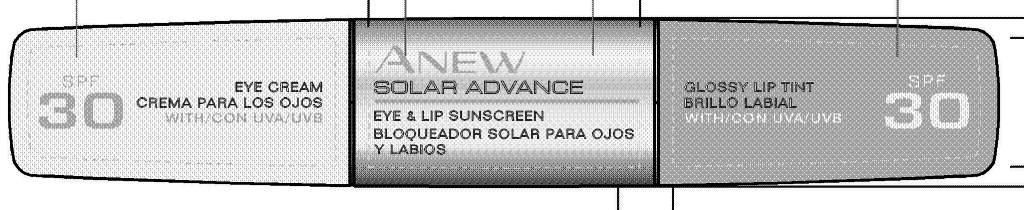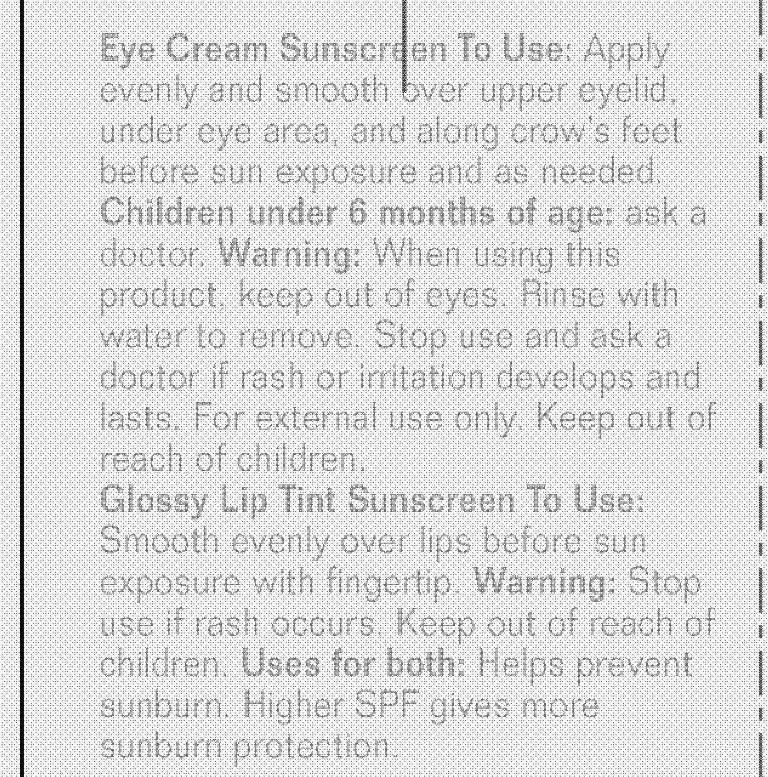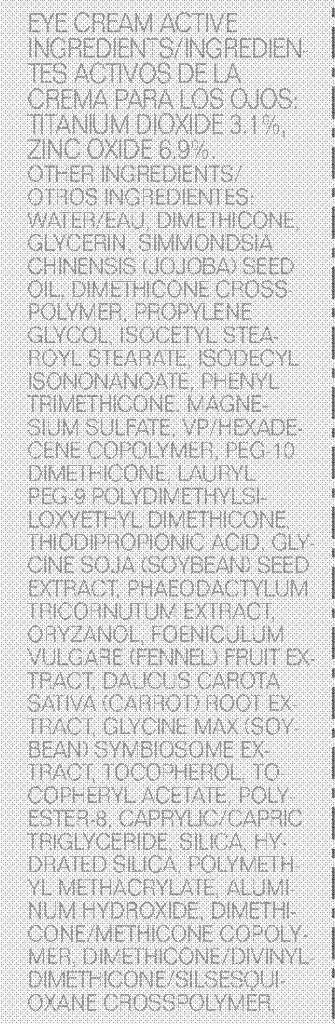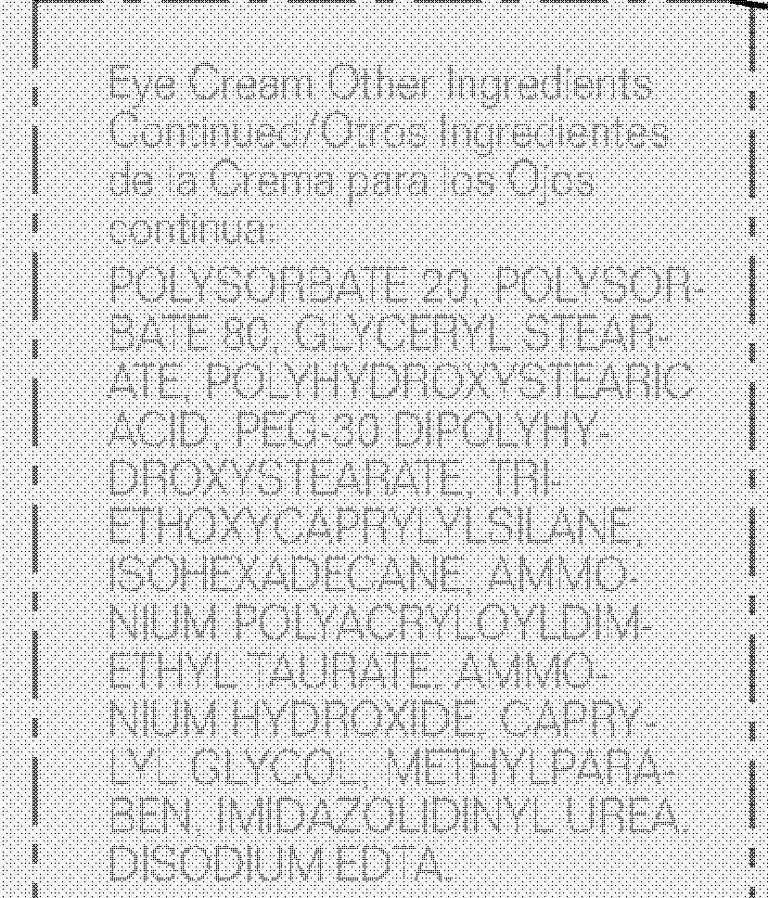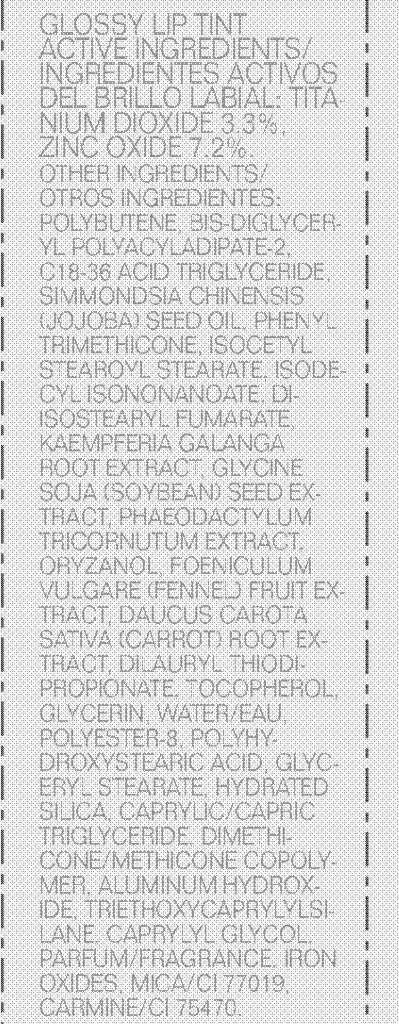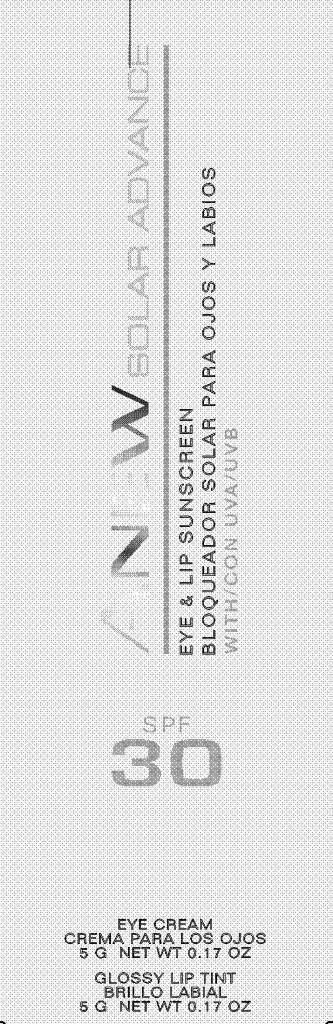 DRUG LABEL: Anew Solar Advance
NDC: 10096-0241 | Form: CREAM
Manufacturer: Avon Products, Inc.
Category: otc | Type: HUMAN OTC DRUG LABEL
Date: 20101221

ACTIVE INGREDIENTS: TITANIUM DIOXIDE 0.155 g/5 g; ZINC OXIDE	 0.345 g/5 g; TITANIUM DIOXIDE 0.165 g/5 g; ZINC OXIDE	 0.36 g/5 g
INACTIVE INGREDIENTS: WATER	; DIMETHICONE	; GLYCERIN	; PROPYLENE GLYCOL	; PHENYL TRIMETHICONE	; HYDRATED SILICA	; ALUMINUM HYDROXIDE	; POLYSORBATE 20	; POLYSORBATE 80	; PEG-30 DIPOLYHYDROXYSTEARATE	; ISOHEXADECANE	; CAPRYLYL GLYCOL	; METHYLPARABEN	; C18-36 ACID TRIGLYCERIDE	; MICA	

DOSAGE AND ADMINISTRATION

Eye Cream Sunscreen To Use: Apply
evenly and smooth over upper eyelid,
under eye area, and along crow’s feet
before sun exposure and as needed.
Children under 6 months of age: ask a
doctor.

WARNINGS

Warning: When using this
product, keep out of eyes. Rinse with
water to remove. Stop use and ask a
doctor if rash or irritation develops and
lasts. For external use only. Keep out of
reach of children.

DOSAGE AND ADMINISTRATION

Glossy Lip Tint Sunscreen To Use:
Smooth evenly over lips before sun
exposure with fingertip.

WARNINGS

Warning: Stop
use if rash occurs. Keep out of reach of
children.

INDICATIONS AND USAGE

Uses for both: Helps prevent
sunburn. Higher SPF gives more
sunburn protection.

EYE CREAM ACTIVE
INGREDIENTS/INGREDIENTES
ACTIVOS DE LA
CREMA PARA LOS OJOS:
TITANIUM DIOXIDE 3.1%,
ZINC OXIDE 6.9%.

INACTIVE INGREDIENT

OTHER INGREDIENTS/
OTROS INGREDIENTES:
WATER/EAU, DIMETHICONE,
GLYCERIN, SIMMONDSIA
CHINENSIS (JOJOBA) SEED
OIL, DIMETHICONE CROSSPOLYMER,
PROPYLENE
GLYCOL, ISOCETYL STEAROYL
STEARATE, ISODECYL
ISONONANOATE, PHENYL
TRIMETHICONE, MAGNESIUM
SULFATE, VP/HEXADECENE
COPOLYMER, PEG-10
DIMETHICONE, LAURYL
PEG-9 POLYDIMETHYLSILOXYETHYL
DIMETHICONE,
THIODIPROPIONIC ACID, GLYCINE
SOJA (SOYBEAN) SEED
EXTRACT, PHAEODACTYLUM
TRICORNUTUM EXTRACT,
ORYZANOL, FOENICULUM
VULGARE (FENNEL) FRUIT EXTRACT,
DAUCUS CAROTA
SATIVA (CARROT) ROOT EXTRACT,
GLYCINE MAX (SOYBEAN)
SYMBIOSOME EXTRACT,
TOCOPHEROL, TOCOPHERYL
ACETATE, POLYESTER-
8, CAPRYLIC/CAPRIC
TRIGLYCERIDE, SILICA, HYDRATED
SILICA, POLYMETHYL
METHACRYLATE, ALUMINUM
HYDROXIDE, DIMETHICONE/
METHICONE COPOLYMER,
DIMETHICONE/DIVINYLDIMETHICONE/
SILSESQUIOXANE
CROSSPOLYMER,POLYSORBATE 20, POLYSORBATE
80, GLYCERYL STEARATE,
POLYHYDROXYSTEARIC
ACID, PEG-30 DIPOLYHYDROXYSTEARATE,
TRIETHOXYCAPRYLYLSILANE,
ISOHEXADECANE, AMMONIUM
POLYACRYLOYLDIMETHYL
TAURATE, AMMONIUM
HYDROXIDE, CAPRYLYL
GLYCOL, METHYLPARABEN,
IMIDAZOLIDINYL UREA,
DISODIUM EDTA.

ACTIVE INGREDIENT

GLOSSY LIP TINT
ACTIVE INGREDIENTS/
INGREDIENTES ACTIVOS
DEL BRILLO LABIAL: TITANIUM
DIOXIDE 3.3%,
ZINC OXIDE 7.2%.

INACTIVE INGREDIENT

OTHER INGREDIENTS/
OTROS INGREDIENTES:
POLYBUTENE, BIS-DIGLYCERYL
POLYACYLADIPATE-2,
C18-36 ACID TRIGLYCERIDE,
SIMMONDSIA CHINENSIS
(JOJOBA) SEED OIL, PHENYL
TRIMETHICONE, ISOCETYL
STEAROYL STEARATE, ISODECYL
ISONONANOATE, DIISOSTEARYL
FUMARATE,
KAEMPFERIA GALANGA
ROOT EXTRACT, GLYCINE
SOJA (SOYBEAN) SEED EXTRACT,
PHAEODACTYLUM
TRICORNUTUM EXTRACT,
ORYZANOL, FOENICULUM
VULGARE (FENNEL) FRUIT EXTRACT,
DAUCUS CAROTA
SATIVA (CARROT) ROOT EXTRACT,
DILAURYL THIODIPROPIONATE,
TOCOPHEROL,
GLYCERIN, WATER/EAU,
POLYESTER-8, POLYHYDROXYSTEARIC
ACID, GLYCERYL
STEARATE, HYDRATED
SILICA, CAPRYLIC/CAPRIC
TRIGLYCERIDE, DIMETHICONE/
METHICONE COPOLYMER,
ALUMINUM HYDROXIDE,
TRIETHOXYCAPRYLYLSILANE,
CAPRYLYL GLYCOL,
PARFUM/FRAGRANCE, IRON
OXIDES, MICA/CI 77019,
CARMINE/CI 75470.